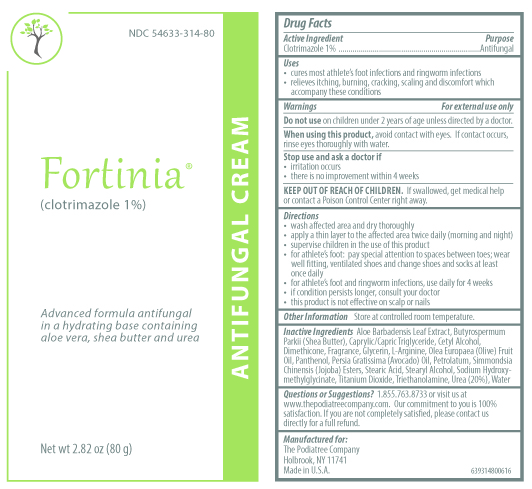 DRUG LABEL: Fortinia
NDC: 54633-314 | Form: CREAM
Manufacturer: The Podiatree Company
Category: otc | Type: HUMAN OTC DRUG LABEL
Date: 20260108

ACTIVE INGREDIENTS: CLOTRIMAZOLE 10 mg/1 g
INACTIVE INGREDIENTS: METHYL L-ARGININE; OLIVE OIL; PANTHENOL; PETROLATUM; STEARYL ALCOHOL; TROLAMINE; UREA; AVOCADO OIL; SODIUM HYDROXYMETHYLGLYCINATE; TITANIUM DIOXIDE; DIMETHICONE 1000; ALOE VERA LEAF; SHEA BUTTER; GLYCERIN; CAPRYLIC/CAPRIC/LINOLEIC TRIGLYCERIDE; WATER; CETYL ALCOHOL; HYDROLYZED JOJOBA ESTERS (ACID FORM); STEARIC ACID

Drug Facts

Active ingredient

Clotrimazole 1%

Purpose

Antifungal

Uses

• cures most athlete’s foot infections and ringworm infections

• relieves itching, burning, cracking, scaling and discomfort which

accompany these conditions

Warnings

For external use only

Do not use on children under 2 years of age unless directed by a doctor.

When using this product avoid contact with eyes. If contact occurs, rinse eyes thoroughly with water.

Stop use and ask a doctor if

- irritation occurs
- there is no improvement within 4 weeks

Keep out of reach of children. If swallowed, get medical help or contact a Poison Control Center right away.

Directions

- wash affected area and dry thoroughly
- apply a thin layer to the affected area twice daily (morning and night)
- supervise children in the use of this product
- for athlete's foot: pay special attention to spaces between toes; wear well-fitting, ventilated shoes and change socks at least once daily
- for athlete's foot and ringworm, use daily for 4 weeks
- if condition persists longer, consult your doctor
- this product is not effective on the scalp or nails

Other information

Store at controlled room temperature

Questions or Suggestions?

1.855.763.8733 or visit us at www.thepodiatreecompany.com. Our commitment to you is 100% satisfaction. If you are not

completely satisfied, please contact us directly for a full refund.

Inactive ingredients

Aloe Barbadensis Leaf Extract, Butyrospermum Parkii (Shea Butter), Caprylic/Capric Triglyceride, Cetyl Alcohol, Dimethicone, Fragrance, Glycerin, L-Arginine, Olea Europaea (Olive) Fruit Oil, Panthenol, Persia Gratissima (Avocado) Oil, Petrolatum, Simmondsia Chinensis (Jojoba) Esters, Stearic Acid, Stearyl Alcohol, Sodium Hydroxymethylglycinate, Titanium Dioxide, Triethanolamine, Urea (20%), Water